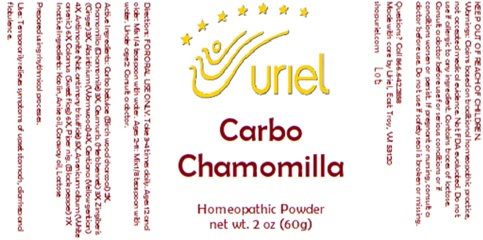 DRUG LABEL: Carbo Chamomilla
NDC: 48951-3275 | Form: POWDER
Manufacturer: Uriel Pharmacy, Inc
Category: homeopathic | Type: HUMAN OTC DRUG LABEL
Date: 20241206

ACTIVE INGREDIENTS: BLACK PEPPER 7 [hp_X]/1 g; WORMWOOD 4 [hp_X]/1 g; GINGER 3 [hp_X]/1 g; GENTIANA LUTEA ROOT 4 [hp_X]/1 g; ANTIMONY TRISULFIDE 5 [hp_X]/1 g; ARSENIC TRIOXIDE 6 [hp_X]/1 g; ACORUS CALAMUS ROOT 6 [hp_X]/1 g; CHARCOAL POWDER 2 [hp_X]/1 g; GEUM URBANUM ROOT 3 [hp_X]/1 g; CHAMOMILE 3 [hp_X]/1 g
INACTIVE INGREDIENTS: ANISE OIL; LACTOSE; KAOLIN; CARAWAY OIL

Carbo Chamomilla

INDICATIONS AND USAGE

Directions: FOR ORAL USE ONLY.

DOSAGE AND ADMINISTRATION

Take 3-4 times daily. Ages 12 and older: Mix 1/4 teaspoon with water. Ages 2-11: Mix 1/8 teaspoon with water. Under age 2: Consult a doctor.

ACTIVE INGREDIENT

Active Ingredients: Carbo betulae (Birch wood charcoal) 2X, Chamomilla (Chamomile) 3X, Geum urb. (Herb bennet) 3X, Zingiberis (Ginger) 3X, Absinthium (Wormwood) 4X, Gentiana (Yellow gentian) 4X, Antimonite (Nat. antimony trisulfide) 5X, Arsenicum album (White arsenic) 6X, Calamus (Sweet flag) 6X, Piper nig. (Black pepper) 7X

Inactive Ingredients: Kaolin, Anise oil, Caraway oil, Lactose

Prepared using rhythmical processes.

PURPOSE

Uses: Temporarily relieves symptoms of upset stomach, diarrhea and flatulence.

KEEP OUT OF REACH OF CHILDREN.

WARNINGS

Warnings: Claims based on traditional homeopathic practice, not accepted medical evidence. Not FDA evaluated. Do not use if allergic to any ingredient. Contains traces of lactose. Consult a doctor before use for serious conditions or if conditions worsen or persist. If pregnant or nursing, consult a doctor before use. Do not use if safety seal is broken or missing.

Questions? Call 866.642.2858
Made with care by Uriel, East Troy, WI 53120
shopuriel.com Lot: